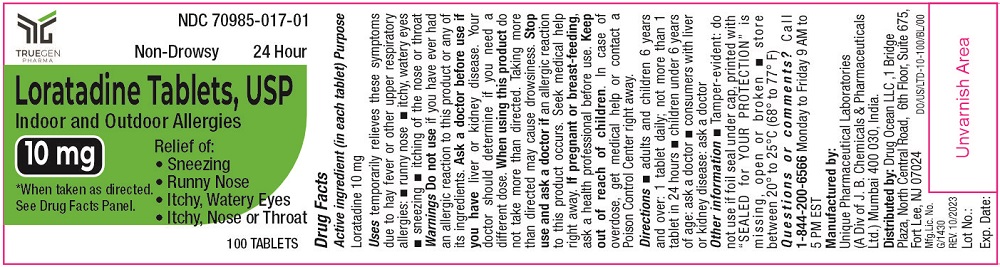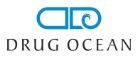 DRUG LABEL: Loratadine
NDC: 70985-017 | Form: TABLET
Manufacturer: DRUG OCEAN LLC
Category: otc | Type: HUMAN OTC DRUG LABEL
Date: 20231020

ACTIVE INGREDIENTS: LORATADINE 10 mg/1 1
INACTIVE INGREDIENTS: LACTOSE MONOHYDRATE; STARCH, CORN; POVIDONE; MAGNESIUM STEARATE

Loratadine Tablets, 10 mg

Active ingredient

Loratadine 10 mg

Purpose

Antihistamine

Uses

temporarily relieves these symptoms due to hay fever or other upper respiratory allergies:

- runny nose
- sneezing
- itchy, water eyes
- itching of the nose or throat

Warnings

Do not use

if you have ever had an allergic reaction to this product or any of its ingredients

Ask a doctor before use if

you have liver or kidney disease. Your doctor should determine if you need a different dose.

When usung this product

do not take more than directed. Taking more than directed may cause drowsiness.

Stop use and ask a doctor if

an allergic reaction to this product occurs. Seek medical help right away.

If pregnant or breast-feeding,

ask a health professional before use

Keep out of reach of children

In case of overdose, get medical help or contact a Poison Control Center right away.

Directions

adults and children 6 years and over | 1 tablet daily; not more than 1 tablet in 24 hours
children under 6 years of age | ask a doctor
consumers with liver or kidney disease | ask a doctor

Other information

- Tamper-evident: do not use if foil under cap is missing, open or broken
- store between 20º to 25ºC (68º to 77ºF)

Inactive ingredients

Lactose monohydrate, magnesium stearate, povidone, starch maize pregelatinized

Questions or comments?

1-844-200-6566 Monday to Friday 9 AM to 5 PM EST

Manufactured by:

Unique Pharmaceutical Laboratories

(A Div. of J. B. Chemicals & Pharmaceuticals Ltd.),

Mumbai 400 030, India.

Distributed by:

Drug Ocean LLC

1 Bridge Plaza, North Central Road,

6th Floor, Suite 675, Fort Lee, NJ 07024

DISPLAY PANEL

NON-DROWSY* 24 Hour

Loratadine Tablets, USP

Indoor and Outdoor Allergies

10mg

Relief of: • Sneezing • Runny Nose • Itchy, Watery Eyes • Itchy, Nose or Throat

*When taken as directed.

See Drug Facts Panel.

100 Tablets